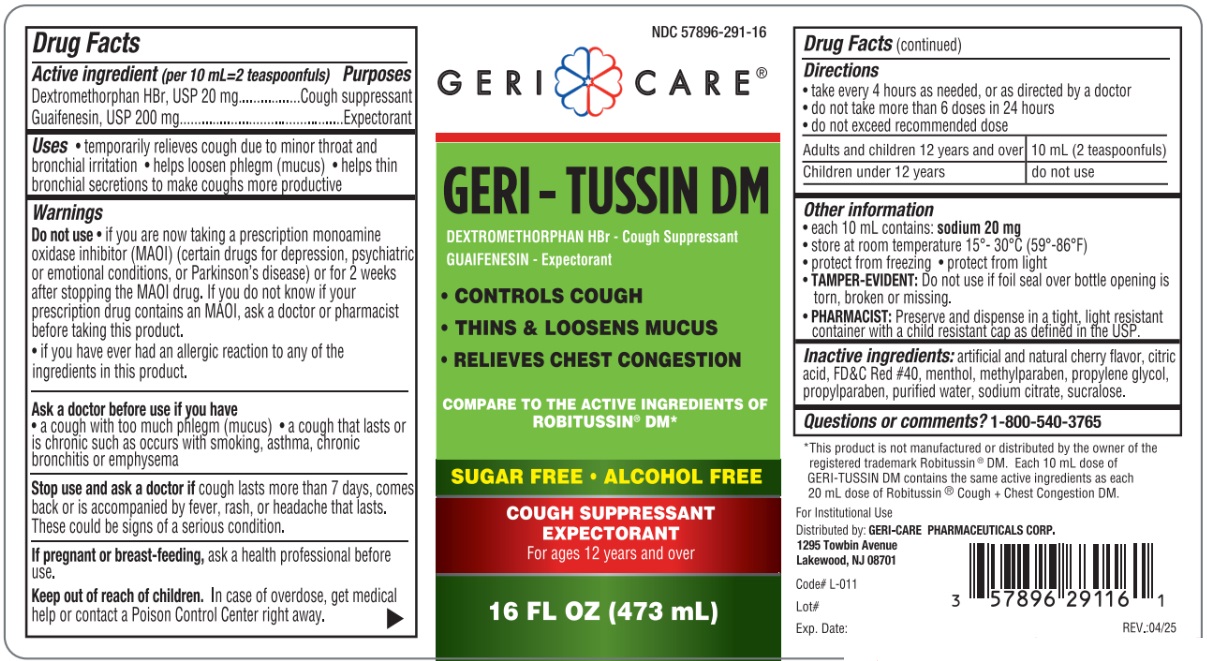 DRUG LABEL: Geri-Tussin
NDC: 57896-291 | Form: LIQUID
Manufacturer: Geri-Care Pharmaceuticals, Corp
Category: otc | Type: HUMAN OTC DRUG LABEL
Date: 20251211

ACTIVE INGREDIENTS: DEXTROMETHORPHAN HYDROBROMIDE 20 mg/10 mL; GUAIFENESIN 200 mg/10 mL
INACTIVE INGREDIENTS: ANHYDROUS CITRIC ACID; FD&C RED NO. 40; METHYLPARABEN; PROPYLENE GLYCOL; PROPYLPARABEN; WATER; SODIUM CITRATE; SUCRALOSE; MENTHOL

GERI-TUSSIN DM

ACTIVE INGREDIENT

in each 10 mL = 2 teaspoonfuls

Dextromethorphan HBr - 20 mg

Guaifenesin - 200 mg

Purpose

Cough suppressant

Expectorant

Uses

- temporarily relieves cough due to minor throat and bronchial irritation
- helps loosen phlegm (mucus)
- helps thin bronchial secretions to make coughs more productive

Warnings

Do not use • if you are now taking a prescription monoamine oxidase inhibitor (MAOI) (certain drugs for depression, psychiatric or emotional conditions, or Parkinson’s disease) or for 2 weeks after stopping the MAOI drug. If you do not know if your prescription drug contains an MAOI, ask a doctor or pharmacist before taking this product.

• if you have ever had an allergic reaction to any of the ingredients in this product.

Ask a doctor before use if you have

- a cough with too much phlegm (mucus)
- a cough that lasts or is chronic such as occurs with smoking, asthma, chronic bronchitis or emphysema

Stop use and ask a doctor if cough lasts more than 7 days, comes back or is accompanied by fever, rash, or headache that lasts. These could be signs of a serious condition.

PREGNANCY OR BREAST FEEDING

If pregnant or breast-feeding, ask a health professional before use.

Keep out of reach of children.In case of overdose, get medical help or contact a Poison Control Center right away.

Directions

- take every 4 hours as needed, or as directed by a doctor
- do not take more than 6 doses in 24 hours
- do not exceed recommended dose

Adults and children 12 years and over | 10 mL (2 teaspoonfuls)
Children under 12 years | do not use

Other information

- each 10 mL contains: sodium 20 mg
- store at room temperature 15°-30°C (59°-86°F)
- protect from freezing
- do not refrigerate
- protect from light
- TAMPER-EVIDENT:Do not use if foil seal over bottle opening is torn, broken or missing.
- PHARMACIST:Preserve and dispense in a tight, light resistant container with a child resistant cap as defined in the USP.

INACTIVE INGREDIENT

Inactive ingredients:artificial and natural cherry flavor, citric acid, FD&C Red #40, menthol, methylparaben, propylene glycol, propylparaben, purified water, sodium citrate, sucralose.

PACKAGE LABEL

Geri Care®

GERI - TUSSIN DM

SUGAR FREE ♦ ALCOHOL FREE

COUGH SUPPRESSANT

EXPECTORANT

For ages 12 years and over

Distributed by: GERI-CARE PHARMACEUTICALS CORP. 1295 Towbin Avenue Lakewood, NJ 08701

Code# L-011

REV.: 05/24